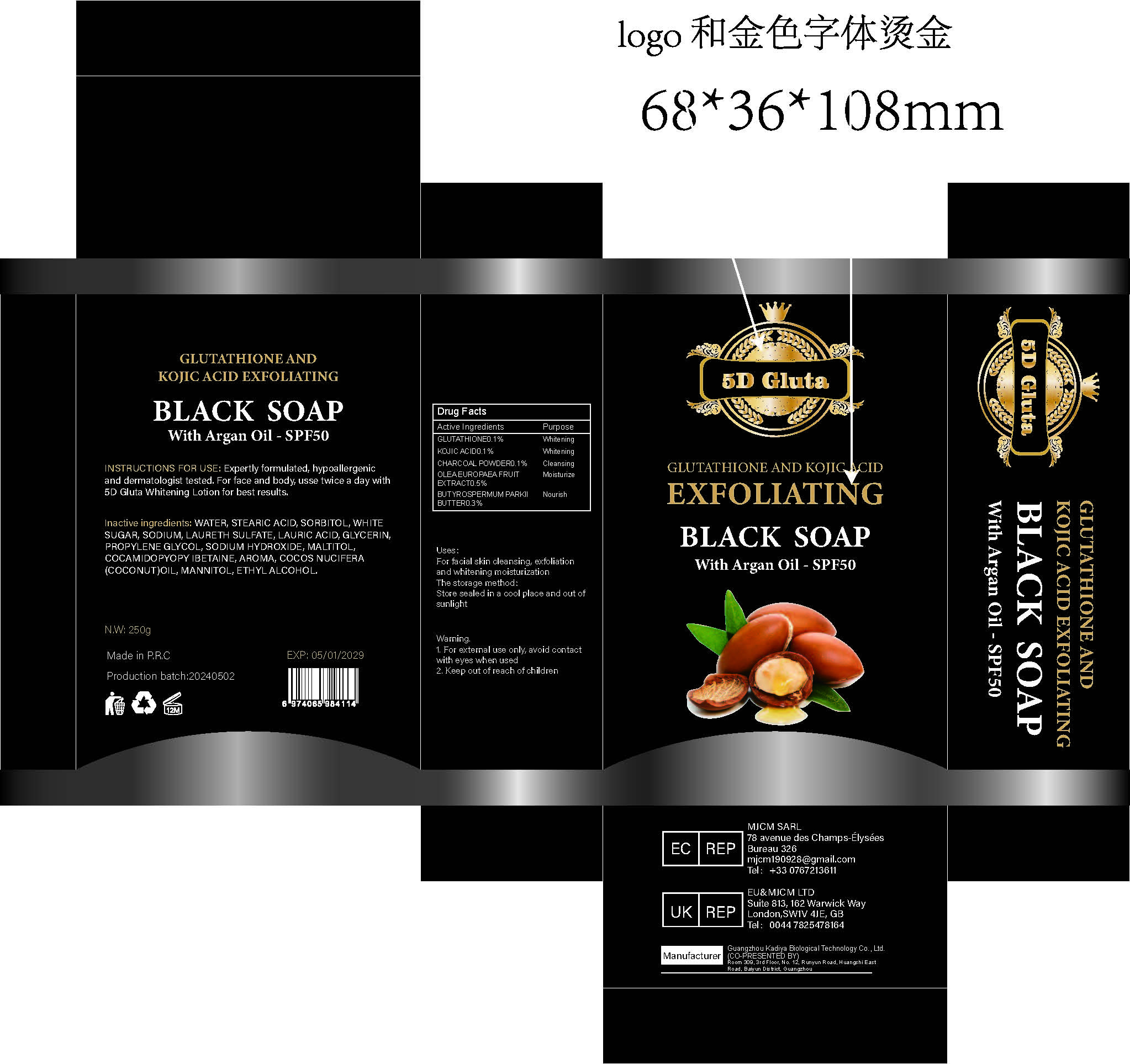 DRUG LABEL: Glutathione And Kojic Atid Exfoliating BlackSoap
NDC: 84423-011 | Form: SOAP
Manufacturer: Guangzhou Kadiya Biotechnology Co., Ltd.
Category: otc | Type: HUMAN OTC DRUG LABEL
Date: 20240708

ACTIVE INGREDIENTS: GLUTATHIONE 0.25 mg/250 mg; ACTIVATED CHARCOAL 0.25 mg/250 mg; KOJIC ACID 0.25 mg/250 mg
INACTIVE INGREDIENTS: MANNITOL; PROPYLENE GLYCOL; COCO/OLEAMIDOPROPYL BETAINE; WATER; STEARIC ACID; SUCROSE; ALCOHOL; SORBITOL; GLYCERIN; SODIUM HYDROXIDE; COCONUT OIL; LAURIC ACID; SODIUM LAURETH SULFATE; MALTITOL

Uses：
For facial skin cleansing, exfoliation and whitening moisturization
Indications: For skin whitening cleansing exfoliation

INACTIVE INGREDIENT

WATER、STEARIC ACID、SORBITOL、WHITE SUGAR、SODIUM、
LAURETH SULFATE、LAURIC ACID、GLYCERIN、PROPYLENE GLYCOL、SODIUM HYDROXIDE、MALTITOL、COCAMIDOPYOPY IBETAINE、AROMA、COCOS NUCIFERA(COCONUT)OIL、MANNITOL、ETHYL ALCOHOL

Warning.
1、For external use only, avoid contact with eyes when used
2、Keep out of reach of children

Uses：
For facial skin cleansing, exfoliation and whitening moisturization
Indications: For skin whitening cleansing exfoliation

KEEP OUT OF REACH OF CHILDREN SECTION

Drug Facts
Active Ingredients
Glutathione 0.1%
KOJIC ACID 0.1%
CHARCOAL POWDER 0.1%
OLEA EUROPAEA FRUIT EXTRACT 0.5%
BUTYROSPERMUM PARKII BUTTER 0.3%

The storage method：
Store sealed in a cool place and out of sunlight

DOSAGE AND ADMINISTRATION

Use twice or three timesa day.

Drug Facts
Active Ingredients
Glutathione 0.1%
KOJIC ACID 0.1%
CHARCOAL POWDER 0.1%
OLEA EUROPAEA FRUIT EXTRACT 0.5%
BUTYROSPERMUM PARKII BUTTER 0.3%

Uses：
For facial skin cleansing, exfoliation and whitening moisturization
Indications: For skin whitening cleansing exfoliation
The storage method：
Store sealed in a cool place and out of sunlight

Warning.
1、For external use only, avoid contact with eyes when used
2、Keep out of reach of children

Inactive ingredients：
WATER、STEARIC ACID、SORBITOL、WHITE SUGAR、SODIUM、
LAURETH SULFATE、LAURIC ACID、GLYCERIN、PROPYLENE GLYCOL、SODIUM HYDROXIDE、MALTITOL、COCAMIDOPYOPY IBETAINE、AROMA、COCOS NUCIFERA(COCONUT)OIL、MANNITOL、ETHYL ALCOHOL